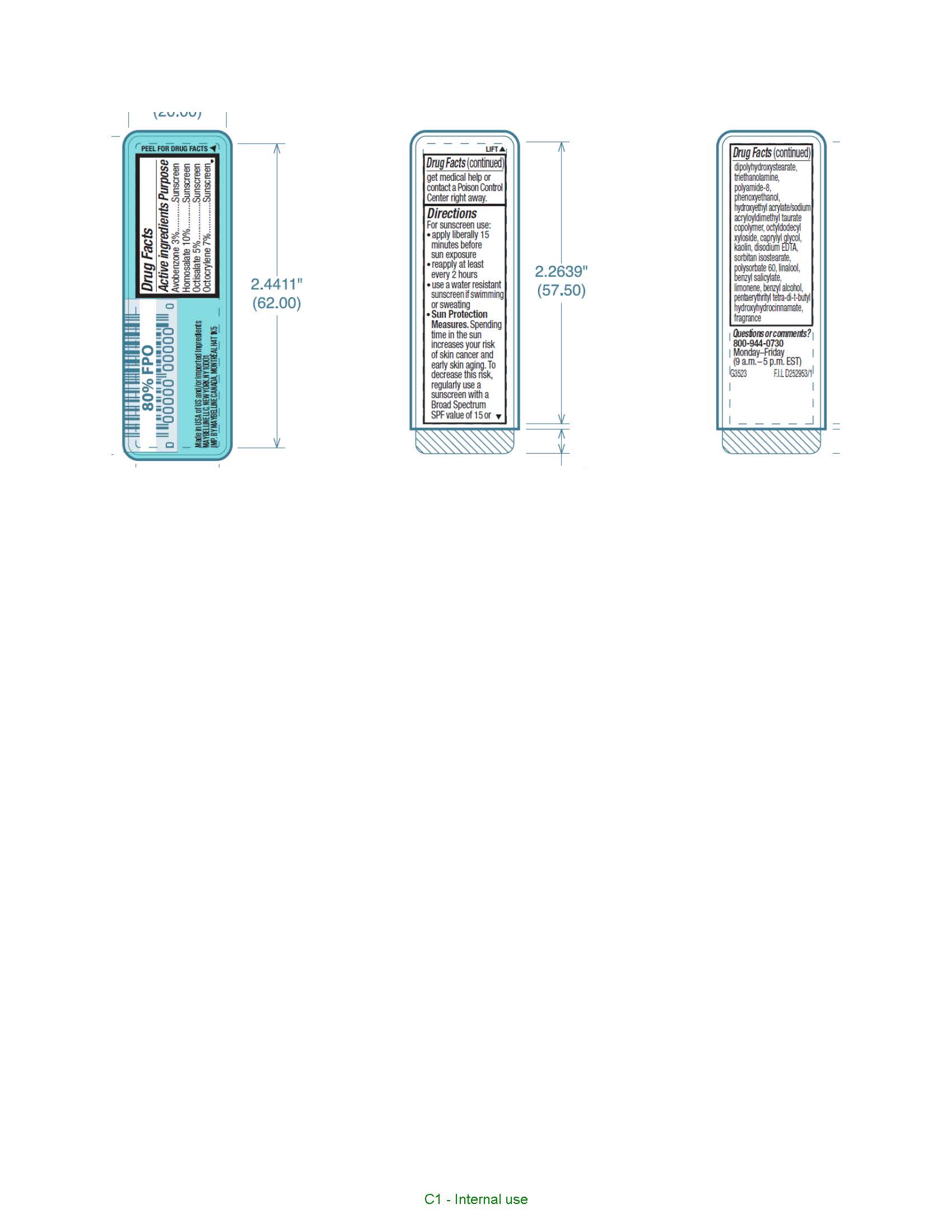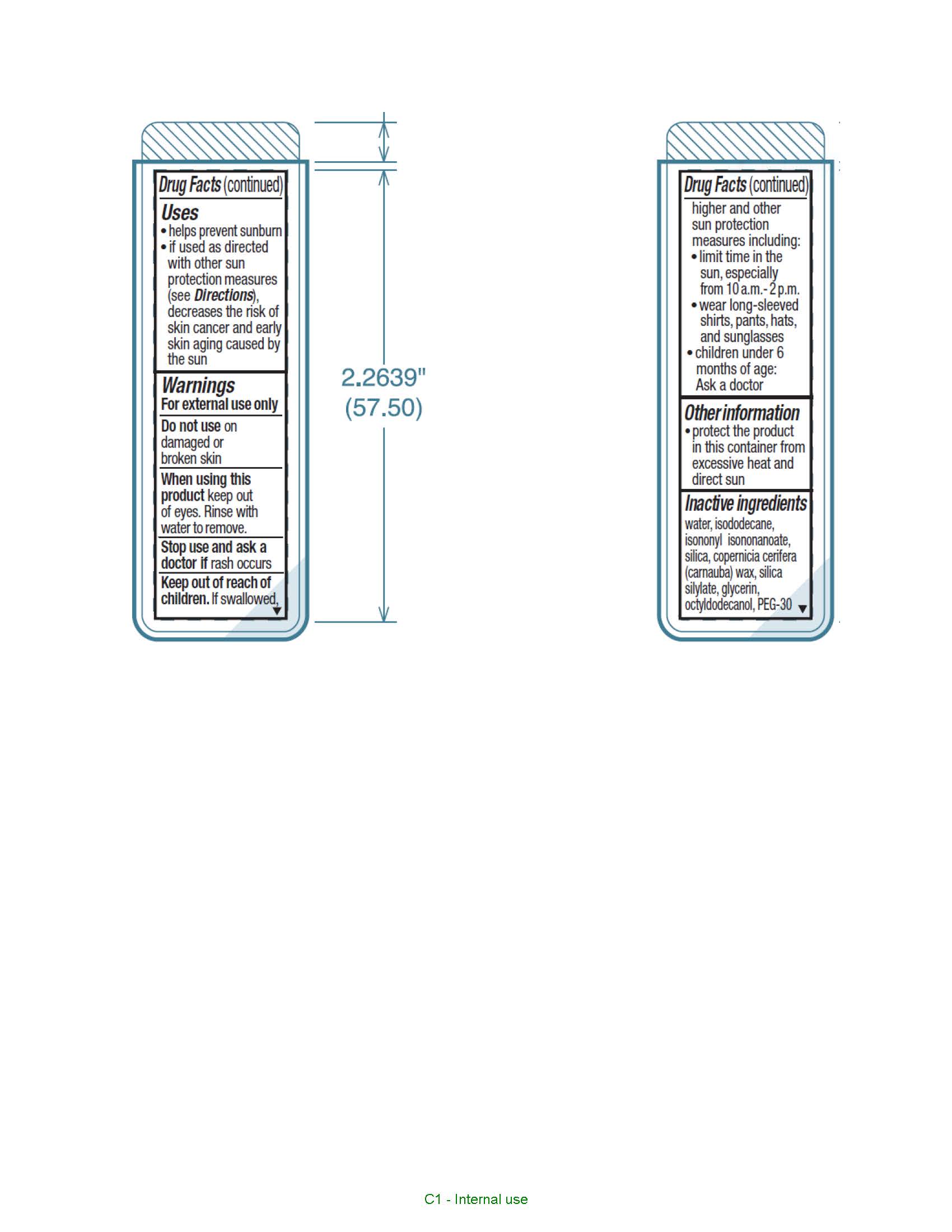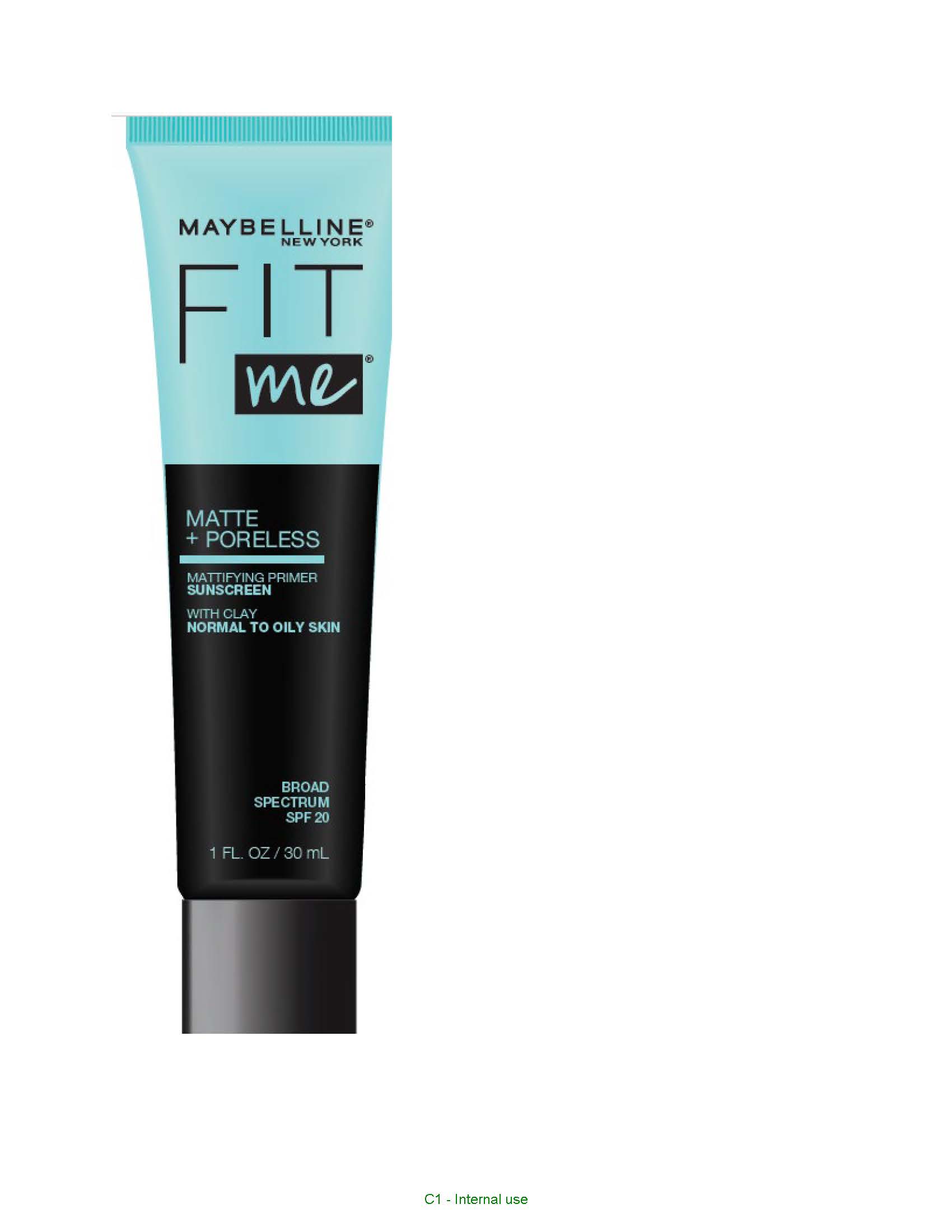 DRUG LABEL: Maybelline New York Fit Me Matte Plus Poreless Mattifying Poreless Primer Broad Spectrum SPF 20 Sunscreen
NDC: 49967-443 | Form: LIQUID
Manufacturer: L'Oreal USA Products Inc
Category: otc | Type: HUMAN OTC DRUG LABEL
Date: 20231228

ACTIVE INGREDIENTS: Avobenzone 30 mg/1 mL; Homosalate 100 mg/1 mL; Octisalate 50 mg/1 mL; Octocrylene 70 mg/1 mL
INACTIVE INGREDIENTS: WATER; ISODODECANE; ISONONYL ISONONANOATE; SILICON DIOXIDE; CARNAUBA WAX; GLYCERIN; OCTYLDODECANOL; PEG-30 DIPOLYHYDROXYSTEARATE; TROLAMINE; POLYAMIDE-8 (4500 MW); PHENOXYETHANOL; HYDROXYETHYL ACRYLATE/SODIUM ACRYLOYLDIMETHYL TAURATE COPOLYMER (100000 MPA.S AT 1.5%); OCTYLDODECYL XYLOSIDE; CAPRYLYL GLYCOL; KAOLIN; EDETATE DISODIUM; SORBITAN ISOSTEARATE; POLYSORBATE 60; LINALOOL, (+/-)-; BENZYL SALICYLATE; LIMONENE, (+)-; BENZYL ALCOHOL; PENTAERYTHRITOL TETRAKIS(3-(3,5-DI-TERT-BUTYL-4-HYDROXYPHENYL)PROPIONATE)

Drug Facts

Active ingredients

Avobenzone 3%

Homosalate 10%

Octisalate 5%

Octocrylene 7%

Purpose

Sunscreen

Uses

- helps prevent sunburn
- if used as directed with other sun protection measures (see Directions), decreases the risk of skin cancer and early skin aging caused by the sun

Warnings

For external use only

Do not use

on damaged or broken skin

When using this product

keep out of eyes. Rinse with water to remove.

Stop use and ask a doctor if

rash occurs

Keep out of reach of children.

If swallowed, get medical help or contact a Poison Control Center right away.

Directions

For sunscreen use:
● apply liberally 15 minutes before sun exposure
● reapply at least every 2 hours
● use a water resistant sunscreen if swimming or sweating
● Sun Protection Measures. Spending time in the sun increases your risk of skin cancer and early skin aging. To decrease this risk, regularly use a sunscreen with a Broad Spectrum SPF value of 15 or higher and other sun protection measures including:
● limit time in the sun, especially from 10 a.m. – 2 p.m.
● wear long-sleeved shirts, pants, hats, and sunglasses
● children under 6 months of age: Ask a doctor

Other information

protect the product in this container from excessive heat and direct sun

Inactive ingredients

water, isododecane, isononyl isononanoate, silica, copernicia cerifera (carnauba) wax, silica silylate, glycerin, octyldodecanol, PEG-30 dipolyhydroxystearate, triethanolamine, polyamide-8, phenoxyethanol, hydroxyethyl acrylate/sodium acryloyldimethyl taurate, copolymer, octyldodecyl xyloside, caprylyl glycol, kaolin, disodium EDTA, sorbitan isostearate, polysorbate 60, linalool, benzyl salicylate, limonene, benzyl alcohol, pentaerythrityl tetra-di-t-butyl hydroxyhydrocinnamate, fragrance